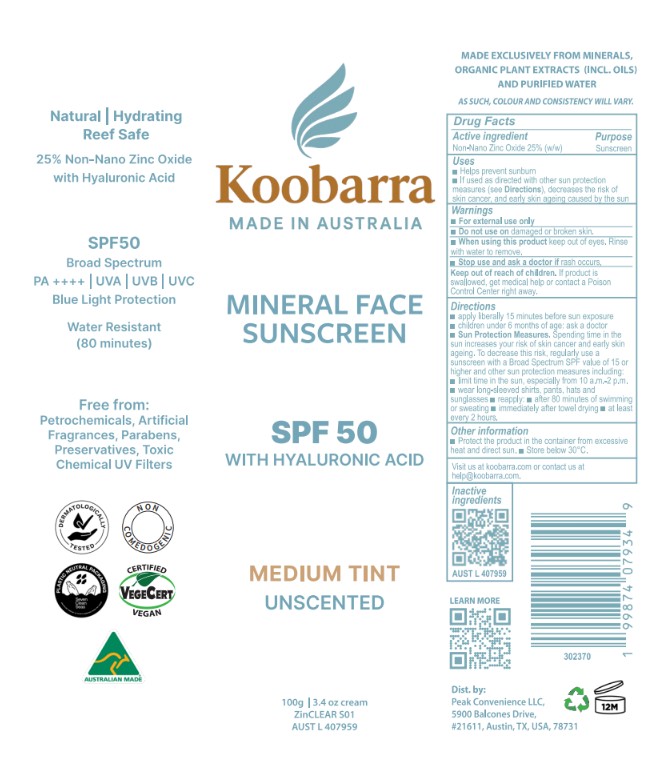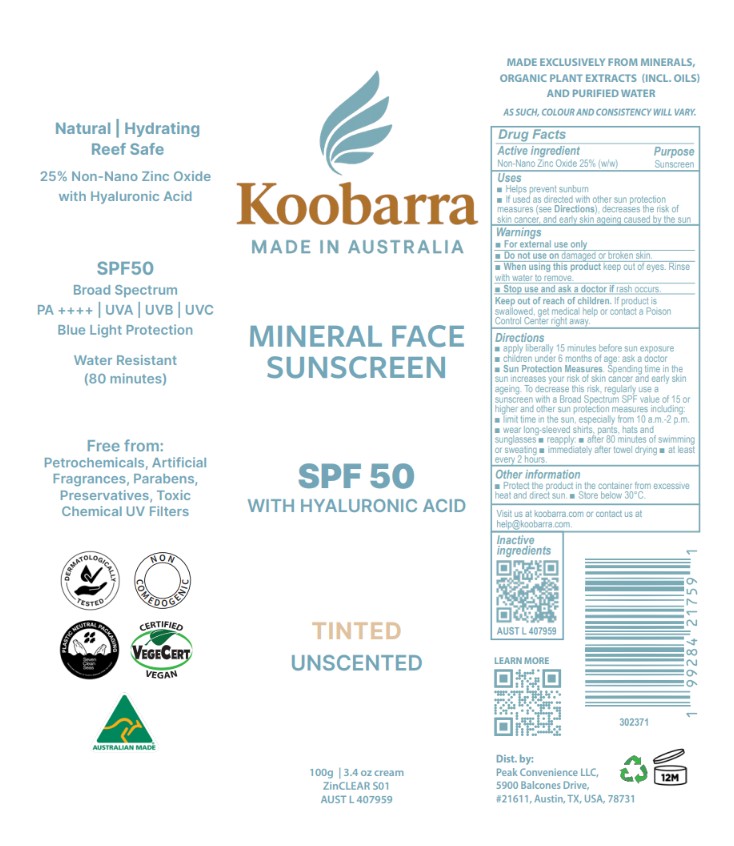 DRUG LABEL: Koobarra Mineral Face Sunscreen SPF 50
NDC: 83252-104 | Form: CREAM
Manufacturer: VEGANIC SKN LIMITED
Category: otc | Type: HUMAN OTC DRUG LABEL
Date: 20260107

ACTIVE INGREDIENTS: ZINC OXIDE 25 kg/100 kg
INACTIVE INGREDIENTS: SODIUM HYALURONATE; SODIUM CHLORIDE; GLYCERIN; POLYGLYCERYL-3 RICINOLEATE; POTASSIUM CETYL PHOSPHATE; CALENDULA OFFICINALIS FLOWERING TOP; SODIUM ASCORBATE; XANTHAN GUM; FERRIC OXIDE RED; BISABOLOL; SODIUM HINOKITIOL; FERRIC OXIDE YELLOW; FERROSOFERRIC OXIDE; CORIANDER OIL; KAKADU PLUM; CITRUS PARADISI (GRAPEFRUIT) SEED OIL; HELIANTHUS ANNUUS (SUNFLOWER) SEED OIL; MALTODEXTRIN; JOJOBA OIL; HIPPOPHAE RHAMNOIDES SEED OIL; TOCOPHEROL; WATER; POLYHYDROXYSTEARIC ACID (2300 MW); ISOSTEARIC ACID; CANDELILLA WAX

Koobarra Mineral Face Sunscreen SPF 50

ACTIVE INGREDIENT

Zinc oxide - 25%

PURPOSE

Sunscreen

INDICATIONS AND USAGE

kindly refer to label picture

WARNINGS

For external use only.

Do not use on damaged r broken skin.

When using this product keep out of eyes. Rinse with water to remove.
Stop use and ask a doctor if rash occurs.

Keep out of reach of children.

If product is swallowed, get medical help or contact a Poison Control Center right away.

Keep out of reach of children.

DOSAGE AND ADMINISTRATION

kindly refer to artwork

INACTIVE INGREDIENT

See ingredients on label